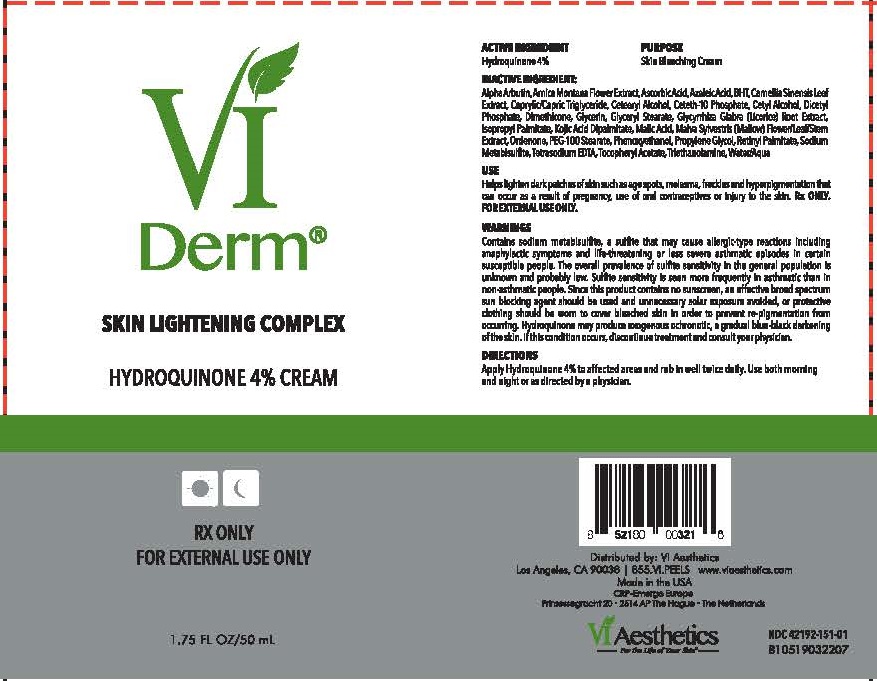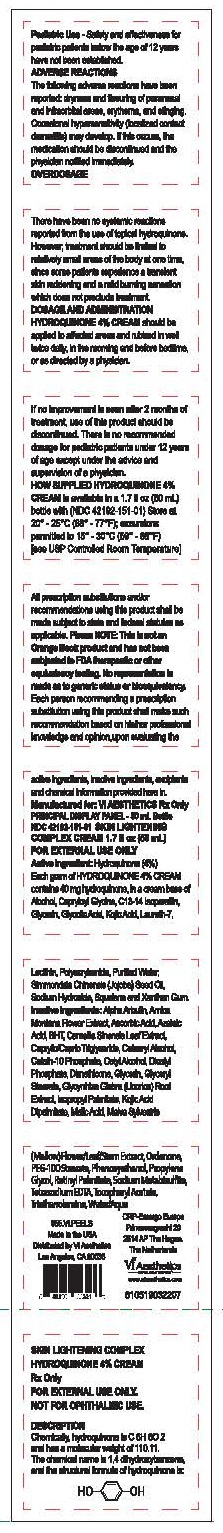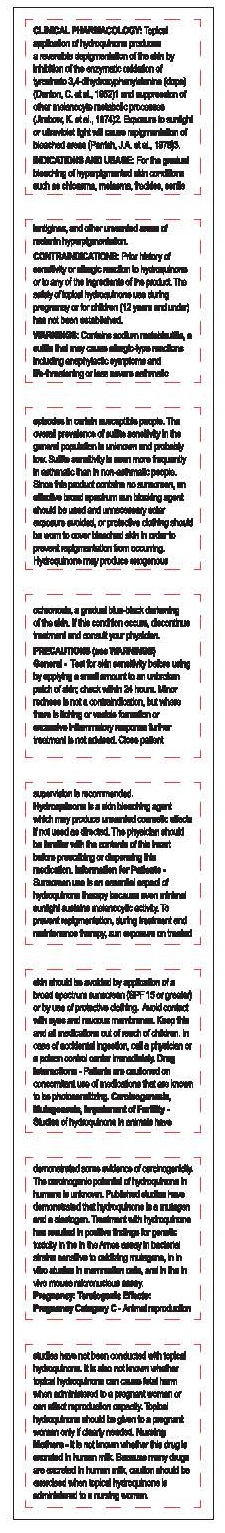 DRUG LABEL: SKIN LIGHTENING COMPLEX
NDC: 70484-101 | Form: CREAM
Manufacturer: Vi Medical Products Inc.
Category: prescription | Type: HUMAN PRESCRIPTION DRUG LABEL
Date: 20190807

ACTIVE INGREDIENTS: HYDROQUINONE 4 g/100 mL
INACTIVE INGREDIENTS: ARBUTIN; ARNICA MONTANA FLOWER; ASCORBIC ACID; AZELAIC ACID; BUTYLATED HYDROXYTOLUENE; GREEN TEA LEAF; MEDIUM-CHAIN TRIGLYCERIDES; CETOSTEARYL ALCOHOL; CETETH-10 PHOSPHATE; CETYL ALCOHOL; DIHEXADECYL PHOSPHATE; DIMETHICONE; GLYCERIN; GLYCERYL MONOSTEARATE; GLYCYRRHIZA GLABRA; ISOPROPYL PALMITATE; KOJIC DIPALMITATE; MALIC ACID; MALVA SYLVESTRIS FLOWERING TOP; METHYL HYDROGENATED ROSINATE; PEG-100 STEARATE; PHENOXYETHANOL; PROPYLENE GLYCOL; VITAMIN A PALMITATE; SODIUM METABISULFITE; EDETATE SODIUM; .ALPHA.-TOCOPHEROL ACETATE; TROLAMINE; WATER

SKIN LIGHTENING COMPLEX

USE

HELPS LIGHTEN DARK PATCHES OF SKIN SUCH AS AGE SPOTS, MELASMA, FRECKLES AND HYPERPIGMENTATION THAT CAN OCCUR AS A RESULT OF PREGNANCY, USE OF ORAL CONTRACEPTIVES OR INJURY TO THE SKIN. RX ONLY. FOR EXTERNAL USE ONLY.